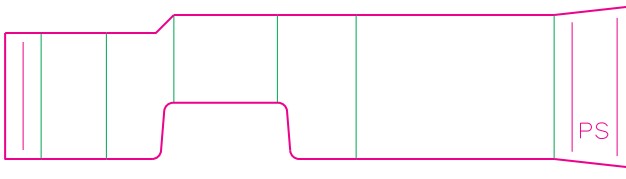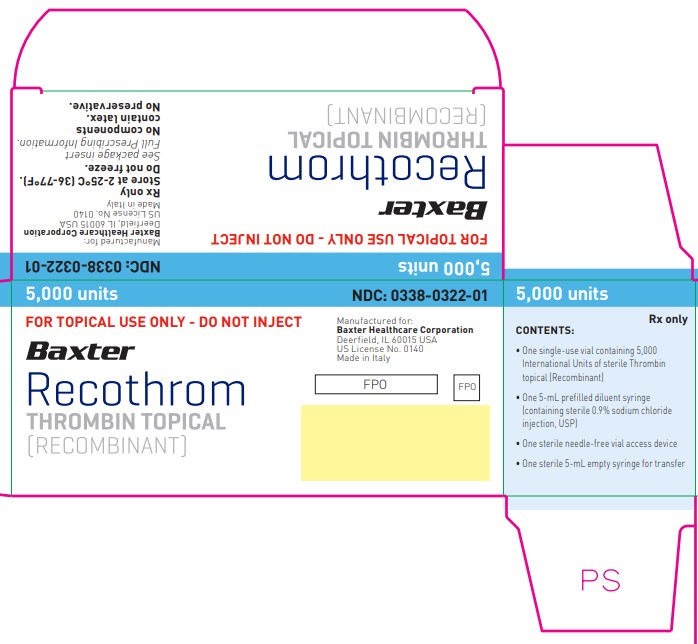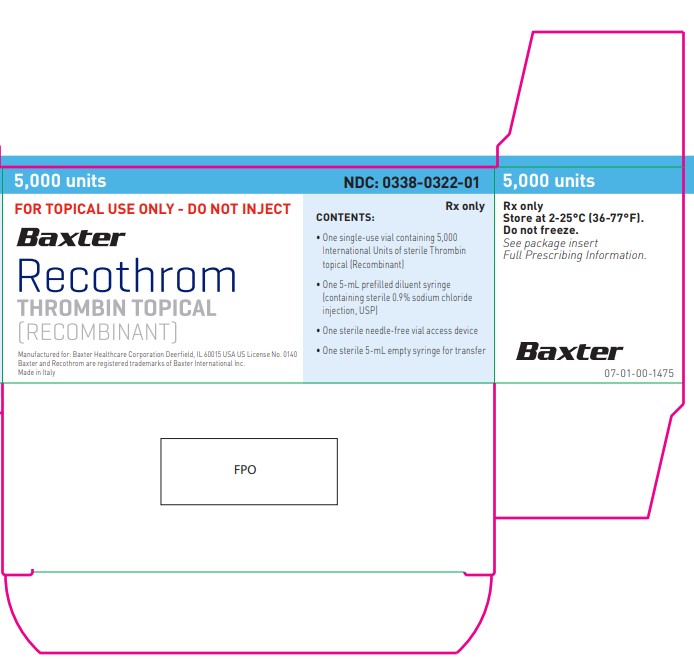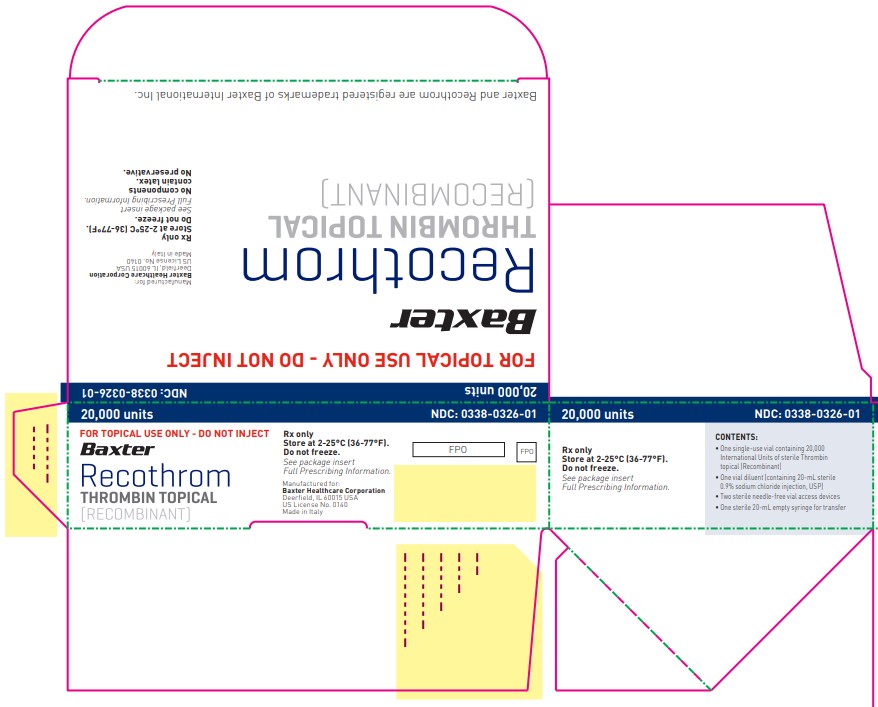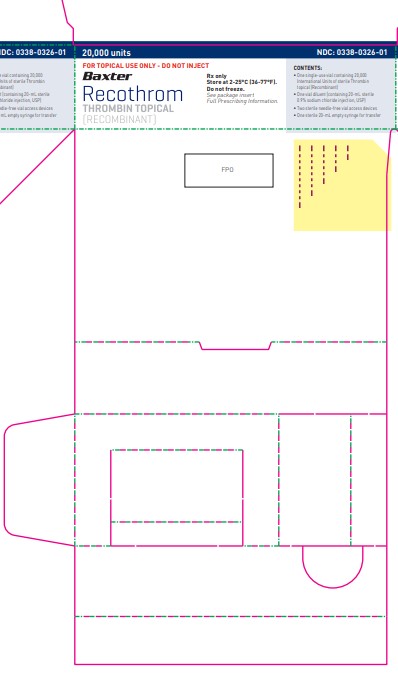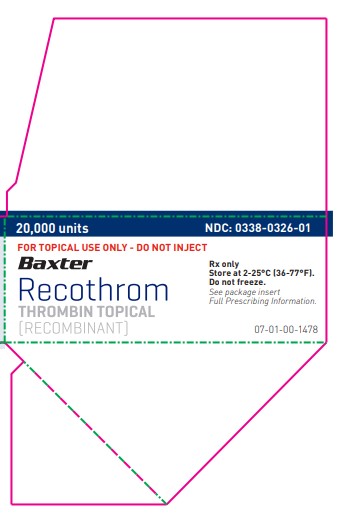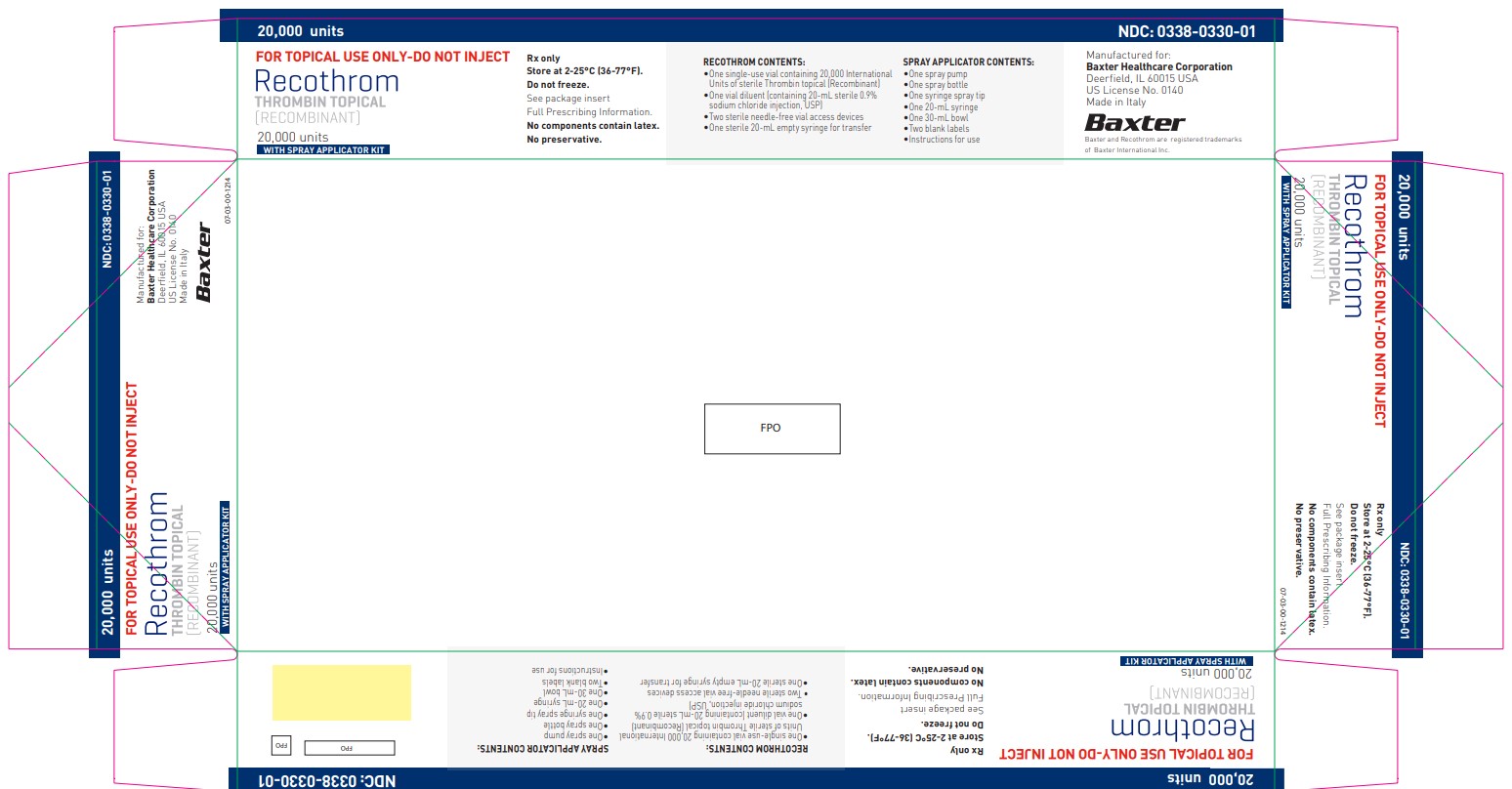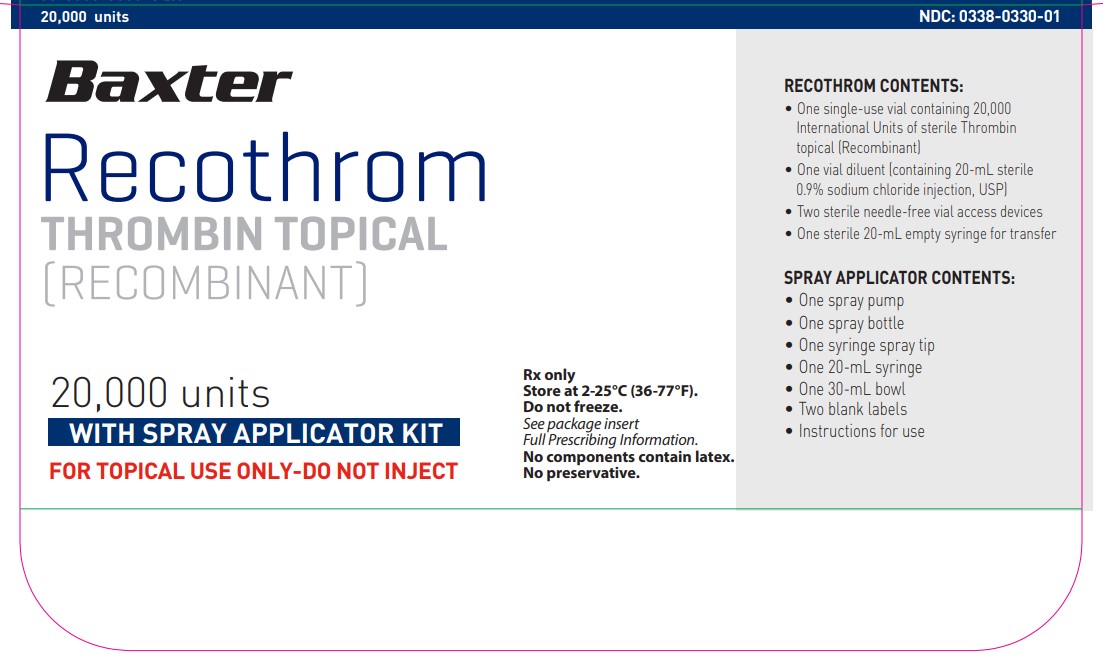 DRUG LABEL: RECOTHROM
NDC: 0338-0322 | Form: KIT | Route: TOPICAL
Manufacturer: Baxter Healthcare Corporation
Category: prescription | Type: HUMAN PRESCRIPTION DRUG LABEL
Date: 20250609

ACTIVE INGREDIENTS: THROMBIN ALFA 1000 [iU]/1 mL
INACTIVE INGREDIENTS: MANNITOL; SUCROSE; SODIUM CHLORIDE; POLYETHYLENE GLYCOL 3350; HISTIDINE; CALCIUM CHLORIDE; SODIUM CHLORIDE

HIGHLIGHTS OF PRESCRIBING INFORMATION

These highlights do not include all the information needed to use RECOTHROM safely and effectively. See full prescribing information for RECOTHROM.
RECOTHROM Thrombin topical (Recombinant)
Lyophilized Powder for Solution – For Topical Use Only
Initial U.S. Approval: 2008

RECENT MAJOR CHANGES

Dosage And Administration (2) 06/2025

1 INDICATIONS AND USAGE

RECOTHROM Thrombin topical (Recombinant), is a topical thrombin indicated to aid hemostasis whenever oozing blood and minor bleeding from capillaries and small venules is accessible and control of bleeding by standard surgical techniques (such as suture, ligature, or cautery) is ineffective or impractical in adults and pediatric populations greater than or equal to one month of age. (1)

RECOTHROM may be used in conjunction with an absorbable gelatin sponge, USP. (1)

2 DOSAGE AND ADMINISTRATION

For topical use only. DO NOT INJECT. (2)

- Reconstitute RECOTHROM Thrombin topical (Recombinant) powder with sterile 0.9% sodium chloride, USP, yielding a solution containing 1,000 units (international units of potency) per mL. (2.1)
- Apply RECOTHROM solution with absorbable gelatin sponge or RECOTHROM Spray Applicator Kit directly to the bleeding site surface. The amount required depends upon the area of tissue to be treated. (2.2)
- 5,000-unit RECOTHROM may be used in conjunction with FLOSEAL NT Hemostatic Matrix, 5mL (2.2)

3 DOSAGE FORMS AND STRENGTHS

RECOTHROM Thrombin topical (Recombinant) is available as 5,000-unit and 20,000-unit vials of sterile recombinant topical thrombin lyophilized powder for solution. When reconstituted as directed, the final solution contains 1,000 units/mL of RECOTHROM. (3)

4 CONTRAINDICATIONS

- Do not inject directly into the circulatory system. (4)
- Do not use for the treatment of massive or brisk arterial bleeding. (4)
- Do not administer to patients with a history of hypersensitivity to RECOTHROM Thrombin topical (Recombinant), any components of RECOTHROM or hamster proteins. (4)

5 WARNINGS AND PRECAUTIONS

- RECOTHROM Thrombin topical (Recombinant) causes thrombosis if it enters the circulatory system. (5.1)
- Hypersensitivity reactions, including anaphylaxis, may occur. (5.2)

6 ADVERSE REACTIONS

- The most common adverse reaction (incidence 6%) was thromboembolic events. (5.1, 6)
- Antibody formation to RECOTHROM Thrombin topical (Recombinant) occurred in <1% of patients. None of the antibodies detected neutralized native human thrombin. (6.2)

To report SUSPECTED ADVERSE REACTIONS, contact Baxter Healthcare at 1-866-888-2472 or FDA at 1-800-FDA-1088 or www.fda.gov/medwatch.

FULL PRESCRIBING INFORMATION

1 INDICATIONS AND USAGE

RECOTHROM Thrombin topical (Recombinant), is a topical thrombin indicated to aid hemostasis whenever oozing blood and minor bleeding from capillaries and small venules is accessible and control of bleeding by standard surgical techniques (such as suture, ligature, or cautery) is ineffective or impractical in adults and pediatric populations greater than or equal to one month of age.

RECOTHROM may be used in conjunction with an absorbable gelatin sponge, USP.

2 DOSAGE AND ADMINISTRATION

For topical use only. DO NOT INJECT.

2.1 Reconstitution of RECOTHROM Thrombin

The volume of reconstituted RECOTHROM Thrombin topical (Recombinant) required will vary depending on the size and number of bleeding sites to be treated and the method of application.

Inspect the integrity of the RECOTHROM package and contents. Do not use if the packaging or contents have been damaged or opened.

Reconstitute the lyophilized powder using the supplied diluent. Use aseptic technique when handling vials and syringes.

5,000-unit RECOTHROM Thrombin topical (Recombinant) Reconstitution

Units used herein represent international units of potency determined using a reference standard that has been calibrated against the World Health Organization Second International Standard for Thrombin.

1. Remove flip-off cap from the top of the RECOTHROM vial.
2. Attach the needle-free vial access device (VAD) and snap it into place on the vial by placing the vial on a flat surface and pushing the VAD straight down into the center of the vial stopper.
3. Attach the prefilled diluent syringe to the VAD.
4. Transfer the 5 mL of diluent from the syringe into the RECOTHROM vial.
5. DO NOT reuse the diluent syringe for transfer of the reconstituted product. Remove and discard the diluent syringe.
6. Gently swirl and invert the RECOTHROM vial until the powder is completely dissolved. Avoid excessive agitation. The powder should dissolve in less than one minute at room temperature. RECOTHROM solution should remain in the vial until ready for transfer to a labeled sterile bowl or basin.
7. Withdraw reconstituted RECOTHROM solution into transfer syringe labeled For topical use only, DO NOT INJECT. Transfer RECOTHROM solution into a labeled sterile bowl or basin.
8. RECOTHROM is ready for application. RECOTHROM is for topical use only – DO NOT INJECT. See Application techniques below (2.2). RECOTHROM is for single use only. Discard unused contents.

20,000-unit RECOTHROM Thrombin topical (Recombinant) Reconstitution

1. Remove the flip-off cap from the top of the RECOTHROM vial and the diluent vial.
2. There are two needle-free vial access devices (VADs) provided. Attach one VAD to the RECOTHROM vial and one VAD to the diluent vial. To attach a VAD to a vial, place the vial on a flat surface and push straight down on the VAD into the center of the vial stopper.
3. Attach the empty 20-mL transfer syringe to the VAD on the diluent vial (injection of air into the diluent vial may facilitate withdrawal of the diluent). This syringe will be used twice: 1. To draw up the diluent from the diluent vial to be transferred into the RECOTHROM vial for reconstitution and 2. To draw up the reconstituted RECOTHROM solution.
4. Draw up 20 mL of diluent from the vial into the syringe.
5. Remove the diluent-filled syringe from the diluent vial and attach the syringe to the VAD on the RECOTHROM vial.
6. Transfer the 20 mL of diluent from the syringe into the RECOTHROM vial.
7. Leave the syringe attached and gently swirl and invert the RECOTHROM vial until the powder is completely dissolved. Avoid excessive agitation. The powder should dissolve in less than one minute at room temperature. RECOTHROM solution should remain in the vial until ready for transfer to a labeled sterile bowl or basin.
8. Withdraw reconstituted RECOTHROM solution into the attached transfer syringe labeled For topical use only, DO NOT INJECT. Use the transfer syringe for immediate transfer of RECOTHROM solution into a labeled sterile bowl or basin.
9. RECOTHROM is ready for application. RECOTHROM is for topical use only—DO NOT INJECT. See Application Techniques below (2.2). RECOTHROM vial is for single use only. Discard unused contents.

2.2 Application Techniques

For topical use only. DO NOT INJECT.

RECOTHROM solution should remain in the vial until ready for transfer to a labeled sterile bowl or basin.

RECOTHROM Thrombin topical (Recombinant) solution is now ready to use, either with an absorbable gelatin sponge, FLOSEAL NT or used with the RECOTHROM Spray Applicator Kit for surface application. DO NOT INJECT.

The amount required depends upon the area of tissue to be treated and the method of application.

Vials are for single use only. Discard unused contents.

Use with Absorbable Gelatin Sponge

Refer to the absorbable gelatin sponge labeling for safety information and instructions on appropriate use.

1. Transfer RECOTHROM solution from transfer syringe labeled For topical use only, DO NOT INJECT to a labeled sterile bowl or basin.
2. Place the desired size pieces of the absorbable gelatin sponge into the bowl containing reconstituted RECOTHROM to completely saturate the sponge(s).
3. Remove the saturated sponge(s) and squeeze gently to remove excess RECOTHROM.
4. Apply the sponge to the bleeding site in a single layer.

Use with RECOTHROM Spray Applicator Kit

The RECOTHROM Spray Applicator Kit is double-packaged to allow for the aseptic transfer of the inner sterile package into a sterile field. Refer to Spray Applicator Kit instructions for use.

Use in conjunction with FLOSEAL NT Hemostatic Matrix, 5mL

1. 5,000-unit RECOTHROM may be used with FLOSEAL NT Hemostatic Matrix, 5mL according to the FLOSEAL NT Hemostatic Matrix, 5mL instructions for use (IFU).

3 DOSAGE FORMS AND STRENGTHS

RECOTHROM Thrombin topical (Recombinant) is available as a sterile lyophilized powder in 5,000- and 20,000-unit single-use vials. When reconstituted with the sterile 0.9% sodium chloride, USP provided, the powder yields a solution containing 1,000 units/mL of Thrombin topical (Recombinant).

4 CONTRAINDICATIONS

- Do not inject directly into the circulatory system.
- Do not use for the treatment of massive or brisk arterial bleeding.
- Do not administer to patients with a history of hypersensitivity to RECOTHROM Thrombin topical (Recombinant) or any components of RECOTHROM.
- Do not use in patients with known hypersensitivity to hamster proteins.

5 WARNINGS AND PRECAUTIONS

5.1 Thrombosis

RECOTHROM Thrombin topical (Recombinant) causes thrombosis if it enters the circulatory system. Apply topically. DO NOT INJECT.

5.2 Hypersensitivity Reactions

Hypersensitivity reactions, including anaphylaxis, may occur.

RECOTHROM Thrombin topical (Recombinant) is produced in a genetically modified Chinese Hamster Ovary (CHO) cell line and may contain hamster or snake proteins [see Contraindications (4) and Description (11)].

6 ADVERSE REACTIONS

Thromboembolic adverse reactions were reported in 6% of surgical patients treated with RECOTHROM Thrombin topical (Recombinant) in all completed clinical trials (N=644) [see Warnings and Precautions (5.1)].

Antibody formation to RECOTHROM occurred in <1% of patients. None of the antibodies detected neutralized native human thrombin [see Adverse Reactions (6.2)].

6.1 Clinical Trials Experience

Because clinical trials are conducted under widely varying conditions, adverse reaction rates observed in the clinical trials of a drug product cannot be directly compared to rates in the clinical trials of another drug and may not reflect the rates observed in clinical practice.

Clinical trials have been performed with RECOTHROM Thrombin topical (Recombinant) applied with absorbable gelatin sponge and applied with a spray applicator. A total of 644 patients were exposed to RECOTHROM in these studies.

RECOTHROM Thrombin topical (Recombinant) Used in Conjunction with Absorbable Gelatin Sponge

Four hundred eleven (411) patients were treated in a randomized, double-blind, controlled trial that compared RECOTHROM to bovine thrombin. Both thrombins were applied with a gelatin sponge in patients undergoing spinal surgery, hepatic resection, peripheral arterial bypass surgery, or arteriovenous graft formation for hemodialysis access.^1 The incidence of thromboembolic adverse reactions was similar between the RECOTHROM and bovine thrombin treatment groups (see Table 1).

Table 1: Incidence of Adverse Reactions with RECOTHROM Thrombin topical (Recombinant) and Bovine Thrombin
Adverse Reaction Category | RECOTHROM; (N=205); n (%) | Bovine Thrombin [THROMBIN-JMI Thrombin, Topical (Bovine)]; (N=206); n (%)
Thromboembolic events | 11 (5%) | 12 (6%)

In an open-label, single-group trial (N=209), patients with documented or highly likely prior exposure to bovine thrombin within the previous three years were treated with RECOTHROM when undergoing surgeries (spinal, peripheral arterial bypass, or arteriovenous graft formation for hemodialysis access).^2 The incidence of thromboembolic adverse reactions in this study was 9%.

In an open-label, single-group trial of re-exposure to RECOTHROM (N=31), patients with documented prior exposure to RECOTHROM were treated with RECOTHROM during surgery (spinal, peripheral arterial bypass, arteriovenous graft formation, or other procedures).^3 The incidence of thromboembolic adverse reactions in this study was 3%.

In other randomized, double-blind trials across a range of surgical settings (N=130; spinal surgery, hepatic resection, peripheral arterial bypass surgery, or arteriovenous graft formation for hemodialysis access), the safety of RECOTHROM (n=88 patients) was compared to placebo (RECOTHROM excipients reconstituted with sterile 0.9% sodium chloride, USP) (n=42 patients). The incidence of thromboembolic adverse reactions in this study was 5% for RECOTHROM and 12% for placebo.

RECOTHROM Thrombin topical (Recombinant) Applied with Spray Applicator

RECOTHROM was applied with a spray applicator in two open-label clinical trials: a single-group trial in adult and pediatric burn patients (N=72; ≤16 years of age, (n=4) and ≥17 years of age, (n=68)) treated with RECOTHROM applied to the wound excision site prior to autologous skin grafting^4; and in a single-group trial in pediatric patients (one month to 17 years of age) undergoing synchronous burn wound excision and autologous skin grafting (N=30; ≤16 years of age, (n=26); ≥17 years of age, (n=4)).^5 In the first study, the incidence of thromboembolic adverse reactions was 1%. In the second study, there were no reported thromboembolic adverse reactions [see Use in Specific Populations (8.4)].

6.2 Immunogenicity

The detection of antibody formation is highly dependent upon the sensitivity and specificity of the assay. The absolute immunogenicity rates reported here are difficult to compare with the results from other products due to differences in assay methodology, patient populations, and other underlying factors.

The potential for development of antibodies to RECOTHROM Thrombin topical (Recombinant) was evaluated in multiple clinical trials and included patients with a single exposure to RECOTHROM as well as patients who were re-exposed to RECOTHROM during a subsequent surgical procedure. Only patients with both baseline and post-treatment antibody specimens available were evaluated for the development of specific anti-RECOTHROM product antibodies, which was defined as seroconversion or a ≥1.0 titer unit (≥10-fold) increase in antibody levels after study treatment. Five of 609 (0.8%; 95% CI, 0.4%-2.8%) evaluable patients developed specific anti-RECOTHROM product antibodies. None of these antibodies were found to neutralize native human thrombin. There was no difference in anti-RECOTHROM product antibody formation incidence among patients exposed to RECOTHROM applied with absorbable gelatin sponge, USP or with spray applicator.

In a clinical trial comparing RECOTHROM to bovine thrombin (N=411; n=398 antibody evaluable) for the development of specific anti-product antibodies, blood samples were collected at baseline and at Day 29 in both treatment groups and were analyzed by ELISA.^1 At baseline, 1.5% of RECOTHROM patients (n=3/198) had positive anti-product antibody titers compared with 5% of bovine thrombin patients (n=10/200). Of these patients, none of the RECOTHROM group and eight in the bovine thrombin group exhibited ≥1.0 titer unit (≥10-fold) increases in anti-product antibody levels after study treatment.

At Day 29, three of 198 (1.5%; 95% CI, 0%-4%) patients in the RECOTHROM group developed specific anti-product antibodies (one patient also developed anti-CHO host cell protein antibodies); 43 of 200 patients in the bovine thrombin group (22%; 95% CI, 16%-28%) developed specific antibodies to bovine thrombin product. Treatment with RECOTHROM resulted in a statistically significant lower incidence of specific anti-product antibody development. Because the study was not powered to detect a difference in clinical outcomes attributable to antibody formation, no conclusions can be drawn regarding the clinical significance of the difference in antibody formation based on the results of this study. None of the antibodies in the RECOTHROM group neutralized native human thrombin. Antibodies against bovine thrombin product were not tested for neutralization of native human thrombin.

In a trial of patients with a high likelihood of prior exposure to bovine thrombin, 15.6% of patients (n=32/205) had anti-bovine thrombin product antibodies and 2% of patients (n=4/200) had anti-RECOTHROM product antibodies at baseline.^2 Following treatment, none of the 200 evaluable patients (patients for whom post-treatment specimens were available) developed antibodies to RECOTHROM.

In a trial of patients previously exposed to RECOTHROM, 31 patients were re-exposed to
RECOTHROM during a subsequent surgery.^3 None of the evaluable patients (n=30) had anti-
RECOTHROM product antibodies at baseline and none developed antibodies at Day 29.

In a trial of RECOTHROM, including 26 pediatric patients (aged one month to 16 years) and four patients 17 years of age, one patient without prior thrombin exposure had pre-existing anti-RECOTHROM product antibodies at baseline.^5 None of the 27 evaluable patients developed anti-RECOTHROM product antibodies at Day 29.

8 USE IN SPECIFIC POPULATIONS

8.1 Pregnancy

Risk Summary
There are no available data regarding RECOTHROM Thrombin topical (Recombinant) in pregnant women. No animal reproductive and developmental toxicity studies have been conducted with RECOTHROM.

In the U.S. general population, the estimated background risk of major birth defects and miscarriage in clinically recognized pregnancies is 2-4% and 15-20%, respectively.

8.2 Lactation

Risk Summary
There is no information regarding the presence of RECOTHROM Thrombin topical (Recombinant) in human milk, the effects on the breastfed infant, and the effects on milk production.

The developmental and health benefits of breastfeeding should be considered along with the mother’s clinical need for RECOTHROM and any potential adverse effects on the breastfed child from RECOTHROM or from underlying maternal condition.

8.4 Pediatric Use

A total of 30 pediatric patients, ages 0 to 16 years (one month to 2 years, n=10; 2 to 12 years, n=12; 12 to 16 years, n=8), were treated in clinical trials with RECOTHROM Thrombin topical (Recombinant) using a spray applicator to burn wound excision sites prior to autologous skin grafting. No patient experienced a thromboembolic adverse reaction. The safety of RECOTHROM in pediatric patients greater than or equal to one month of age is supported by these data and by extrapolation of efficacy from adequate and well-controlled studies of RECOTHROM in adults. Safety and efficacy have not been established in neonates [see Adverse Reactions (6)].

8.5 Geriatric Use

Of 644 patients in clinical studies of RECOTHROM Thrombin topical (Recombinant), 36% (n=232/644) were ≥65 years old and 15% (n=95/644) were ≥75 years old.

No differences in safety or effectiveness were observed between these patients and younger patients, and other reported clinical experience has not identified differences in responses between the elderly and younger patients, but greater sensitivity of some older individuals cannot be ruled out.

11 DESCRIPTION

RECOTHROM Thrombin topical (Recombinant), is a human coagulation protein produced via recombinant DNA technology from a genetically modified CHO cell line. RECOTHROM is identical in amino acid sequence and structurally similar to naturally occurring human thrombin. RECOTHROM precursor is secreted to culture medium as single chain form that is proteolytically converted to a two-chain active form (using a protein derived from snakes) and is purified by a chromatographic process that yields a product having hemostatic activities similar to native human thrombin. The cell line used to manufacture RECOTHROM has been tested and shown to be free of known infectious agents. The cell culture process used in the manufacture of RECOTHROM employs no additives of human or animal origin. The purification process includes solvent-detergent treatment and nano-filtration steps dedicated to viral clearance.

RECOTHROM is provided as a sterile, white to off-white, preservative-free, lyophilized powder in vials for reconstitution with diluent (sterile 0.9% sodium chloride, USP). Reconstitution with the provided diluent, as described [see Dosage and Administration (2.1)], yields a solution with a pH of 6.0 containing 1,000 units/mL of recombinant thrombin for topical use. The formulated product is a clear, colorless solution upon reconstitution and contains the following excipients: histidine, mannitol, sucrose, polyethylene glycol 3350, sodium chloride, and calcium chloride dihydrate, USP.

12 CLINICAL PHARMACOLOGY

12.1 Mechanism of Action

RECOTHROM Thrombin topical (Recombinant), is a specific human serine protease that promotes hemostasis and acts locally when applied topically to a site of bleeding.

RECOTHROM activates platelets and catalyzes the conversion of fibrinogen to fibrin, which are steps that are essential for blood clot formation.

13 NONCLINICAL TOXICOLOGY

13.1 Carcinogenesis, Mutagenesis, Impairment of Fertility

In vitro cytotoxicity studies have been performed in mouse L929 fibroblast cell cultures and
demonstrate a concentration-dependent effect on cell morphology. The thrombin-induced
morphological changes were similar to those seen with bovine thrombin.

13.2 Animal Toxicology and/or Pharmacology

In a study in nonhuman primates, RECOTHROM Thrombin topical (Recombinant) was applied directly to a liver wound with an absorbable gelatin sponge, USP. In a second study, RECOTHROM was administered subcutaneously once weekly for four weeks to nonhuman primates following repeat doses of 5405 units/m^2. In both studies, RECOTHROM had no effect on clinical signs, serum chemistry, coagulation parameters, or histopathology; only normal postsurgical findings were observed. No animals developed anti-RECOTHROM product antibodies in either study.

RECOTHROM was found to be non-irritating when instilled in the eyes (200 units) or applied to normal or abraded skin of rabbits (up to 1,000 units/site).

To evaluate RECOTHROM inhibition and clearance from the bloodstream, radiolabeled RECOTHROM was administered intravenously or subcutaneously to nonhuman primates and applied with an absorbable gelatin sponge, USP, in a rabbit hepatic wound model. RECOTHROM did not circulate in the blood as free, active molecule, but was rapidly inactivated (<5 minutes) after formation of complexes with endogenous inhibitors (e.g., antithrombin III); these complexes were cleared by the liver. RECOTHROM applied with an absorbable gelatin sponge, USP, was shown to decrease time to hemostasis (TTH) when compared to saline in a rabbit hepatic wound model and rat heminephrectomy model. RECOTHROM also reduced TTH when directly applied in a porcine partial-thickness excisional skin-wound model as compared to saline control (or no treatment).

RECOTHROM applied with a gauze sponge decreased TTH in a concentration-dependent manner in both the rabbit and rat models. Concentrations of RECOTHROM >1,000 units/mL were no different than 1,000 units/mL while the effect of RECOTHROM diluted to a concentration of 100 units/mL on TTH was indistinguishable from placebo.

The performance of RECOTHROM mixed with gelatin matrix (FLOSEAL NT Hemostatic Matrix, 5mL) was compared to FLOSEAL Hemostatic Matrix, 5mL (human plasma-derived thrombin mixed with gelatin matrix) in a blinded nonclinical study using a heparinized porcine liver punch model of moderate to severe bleeding. The analysis demonstrated that the performance of RECOTHROM mixed with gelatin matrix was non-inferior to human plasma-derived thrombin mixed with gelatin matrix.

14 CLINICAL STUDIES

RECOTHROM Thrombin topical (Recombinant) was evaluated in a randomized, double-blind comparative clinical trial to bovine thrombin. Each thrombin was topically applied to bleeding sites with an absorbable gelatin sponge at a nominal concentration of 1,000 units/mL.^1 Patients (N=411) were a heterogeneous surgical population undergoing surgery in one of four surgical settings: spinal surgery (n=122, 30%), hepatic resection (n=125, 30%), peripheral arterial bypass surgery (n=88, 21%), and arteriovenous graft formation for hemodialysis access (n=76, 18%). Patients with prior heparin-induced thrombocytopenia were excluded. Patient ages ranged from 21 to 89 years, gender was 53% male and 47% female, and the distribution by race was 68% white, 18% black or African American, and 14% other. The distribution of these characteristics was similar in both the RECOTHROM and bovine thrombin treatment groups.

The objectives of the study were to evaluate the comparative efficacy, safety, and immunogenicity of RECOTHROM and bovine thrombin in combination with an absorbable gelatin sponge as adjuncts to hemostasis in surgery. Efficacy was evaluated by the incidence of hemostasis within 10 minutes. Bleeding appropriate for evaluation was defined as mild to moderate bleeding, either on its own or remaining after brisk bleeding was controlled by standard surgical modalities. Although multiple bleeding sites could be treated, only one bleeding site per patient was selected to determine effectiveness.

Table 2 summarizes the incidence of hemostasis within 10 minutes for each treatment for the 401
efficacy evaluable patients. The incidence of hemostasis within 10 minutes was comparable for the
RECOTHROM and bovine thrombin groups.

Table 2: Hemostasis Within 10 Minutes [Evaluation of hemostasis at ≤ 10 minutes for patients treated at 1 of 4 primary TTH bleeding site types: epidural venous plexus, hepatic resection site, peripheral arterial bypass proximal anastomosis, and arteriovenous graft arterial anastomosis.]
 | RECOTHROM; (N=198); (%) | Bovine Thrombin [THROMBIN-JMI Thrombin, Topical (Bovine)]; (N=203); (%)
Overall | 95% | 95%
Spinal surgery | 98% | 98%
Hepatic resection | 98% | 97%
Peripheral arterial bypass | 85% | 86%
Arteriovenous graft formation | 97% | 97%

The percentage of patients achieving hemostasis at 1.5, 3, 6, and 10 minutes is listed in Table 3.

Table 3: Cumulative Incidence of Hemostasis Over Time
Time (Minutes) | RECOTHROM; (N=198); (%) | Bovine Thrombin [THROMBIN-JMI Thrombin, Topical (Bovine)]; (N=203); (%)
1.5 | 48% | 46%
3 | 81% | 72%
6 | 92% | 88%
10 | 95% | 95%

15 REFERENCES

1. Chapman WC, Singla N, Genyk Y, et al. A phase 3, randomized, double-blind comparative study of the efficacy and safety of topical recombinant human thrombin and bovine thrombin in surgical hemostasis. J Am Coll Surg. 2007;205(2):256-265.
2. Singla NK, Ballard JL, Moneta G, et al. A phase 3b open-label, single-group immunogenicity and safety study of topical recombinant thrombin in surgical hemostasis. J Am Coll Surg. 2009;209(1):68-74.
3. Singla NK, Gasparis AP, Ballard JL, et al. Immunogenicity and safety of re-exposure to recombinant human thrombin in surgical hemostasis. J Am Coll Surg. 2011;213(6):722-727.
4. Greenhalgh DG, Gamelli RL, Collins J, et al. Recombinant thrombin: safety and immunogenicity in burn wound excision and grafting. J Burn Care Res. 2009;30(3):371-379.
5. Foster KN, Mullins RF, Greenhalgh DG, et al. Recombinant human thrombin: safety and immunogenicity in pediatric burn wound excision. J Ped Surg. 2011;46(10):1992-1999.

16 HOW SUPPLIED/STORAGE AND HANDLING

RECOTHROM Thrombin topical (Recombinant), is supplied in single-use, preservative-free vials in the following packages:

NDC 0338-0322-01
A 5,000-unit vial of RECOTHROM with a 5-mL prefilled diluent syringe (containing sterile 0.9% sodium chloride, USP), a sterile needle-free vial access device, and a 5-mL sterile empty transfer syringe.

NDC 0338-0326-01
A 20,000-unit vial of RECOTHROM with a 20-mL vial of diluent (containing sterile 0.9% sodium chloride, USP), 2 sterile needle-free vial access devices, and a 20-mL sterile empty transfer syringe.

NDC 0338-0330-01
The 20,000-unit RECOTHROM kit co-packaged with RECOTHROM Spray Applicator Kit.

No RECOTHROM kit components contain latex.

Store RECOTHROM sterile powder vials at 2°C to 25°C (36°F to 77°F). Do not freeze.

Reconstituted solutions of RECOTHROM prepared with sterile 0.9% sodium chloride, USP, may be stored for up to 24 hours at 2°C to 25°C (36°F to 77°F). Discard reconstituted solution after 24 hours.

17 PATIENT COUNSELING INFORMATION

Because topical thrombin may cause the formation of clots in blood vessels if absorbed systemically, advise patients to consult their physician if they experience leg tenderness or swelling, chest pain, shortness of breath, or difficulty speaking or swallowing [see Warnings and Precautions (5.1)].

Baxter and Recothrom are registered trademarks of Baxter International Inc.
Thrombin-JMI is a registered trademark of King Pharmaceuticals Research and Development, LLC.

Manufactured for:
Baxter Healthcare Corporation
Deerfield, IL 60015 USA
US License No. 0140

0719007359

PACKAGE/LABEL PRINCIPAL DISPLAY PANEL

Carton Label

PS
5,000 units
NDC: 0338-0322-01

FOR TOPICAL USE ONLY - DO NOT INJECT

Baxter Logo

RECOTHROM
THROMBIN TOPICAL
(RECOMBINANT)

Manufactured for:
Baxter Healthcare Corporation
Deerfield, IL 60015 USA
US License No. 0140
Made in Italy

FPO

FPO

5,000 units

Rx only

CONTENTS:

• One single-use vial containing 5,000 International Units of sterile Thrombin topical (Recombinant)

• One 5-mL prefilled diluent syringe (containing sterile 0.9% sodium chloride injection, USP)

• One sterile needle-free transfer device

• One sterile 5-mL empty syringe for transfer

PS

5,000 units
NDC: 0338-0322-01

FOR TOPICAL USE ONLY - DO NOT INJECT

Baxter Logo

RECOTHROM
THROMBIN TOPICAL
(RECOMBINANT)

Manufactured for: Baxter Healthcare Corporation Deerfield, IL 60015 USA US License No. 0140 Baxter and Recothrom are registered trademarks of Baxter International Inc. Made in Italy

Rx only

CONTENTS:

• One single-use vial containing 5,000 International Units of sterile Thrombin topical (Recombinant)

• One 5-mL prefilled diluent syringe (containing sterile 0.9% sodium chloride injection, USP)

• One sterile needle-free transfer device

• One sterile 5-mL empty syringe for transfer

FPO

5,000 UNITS

Rx only
Store at 2-25°C (36-77°F).
Do not freeze.
See package insert
Full Prescribing Information.

Baxter Logo

07-01-00-1475

5,000 units
NDC: 0338-0322-01

FOR TOPICAL USE ONLY - DO NOT INJECT

Baxter Logo

RECOTHROM
THROMBIN TOPICAL
(RECOMBINANT)

Manufactured for:
Baxter Healthcare Corporation
Deerfield, IL 60015 USA
US License No. 0140
Made in Italy
Rx only
Store at 2-25°C (36-77°F).
Do not freeze.
See package insert
Full Prescribing Information.
No components
contain latex.
No preservative.

Carton Label

20,000 units
NDC: 0338-0326-01

FOR TOPICAL USE ONLY - DO NOT INJECT

Baxter Logo

RECOTHROM
THROMBIN TOPICAL
(RECOMBINANT)

Rx only
Store at 2-25°C (36-77°F).
Do not freeze.
See package insert
Full Prescribing Information.

Manufactured for:
Baxter Healthcare Corporation
Deerfield, IL 60015 USA
US License No. 0140
Made in Italy

FPO

FPO

20,000 units
NDC: 0338-0326-01

Rx only
Store at 2-25°C (36-77°F).
Do not freeze.
See package insert
Full Prescribing Information.

CONTENTS:

• One single-use vial containing 20,000
International Units of sterile Thrombin
topical (Recombinant)

• One vial diluent (containing 20-mL sterile
0.9% sodium chloride injection, USP)

• Two sterile needle-free transfer devices

• One sterile 20-mL empty syringe for transfer

20,000 units
NDC: 0338-0326-01

FOR TOPICAL USE ONLY - DO NOT INJECT

Baxter Logo

RECOTHROM
THROMBIN TOPICAL
(RECOMBINANT)

Rx only
Store at 2-25°C (36-77°F).
Do not freeze.
See package insert
Full Prescribing Information.

CONTENTS:

• One single-use vial containing 20,000
International Units of sterile Thrombin
topical (Recombinant)

• One vial diluent (containing 20-mL sterile
0.9% sodium chloride injection, USP)

• Two sterile needle-free transfer devices

• One sterile 20-mL empty syringe for transfer

FPO

20,000 units
NDC: 0338-0326-01

FOR TOPICAL USE ONLY - DO NOT INJECT

Baxter Logo

RECOTHROM
THROMBIN TOPICAL
(RECOMBINANT)

Rx only
Store at 2-25°C (36-77°F).
Do not freeze.
See package insert
Full Prescribing Information.

07-01-00-1478

20,000 units
NDC: 0338-0326-01

FOR TOPICAL USE ONLY - DO NOT INJECT

Baxter Logo

RECOTHROM
THROMBIN TOPICAL
(RECOMBINANT)

Manufactured for:
Baxter Healthcare Corporation
Deerfield, IL 60015 USA
US License No. 0140
Made in Italy

Rx only
Store at 2-25°C (36-77°F).
Do not freeze.
See package insert
Full Prescribing Information.

No Components
contain latex.
No preservative.

Baxter and Recothrom are registered trademarks of Baxter International Inc.

Carton Label

20,000 units
NDC: 0338-0330-01

FOR TOPICAL USE ONLY - DO NOT INJECT

RECOTHROM
THROMBIN TOPICAL
(RECOMBINANT)

20,000 units

WITH SPRAY APPLICATOR KIT

Rx only
Store at 2-25°C (36-77°F).
Do not freeze.
See package insert
Full Prescribing Information.
No components contain latex.
No preservative.

RECOTHROM CONTENTS:
• One single-use vial containing 20,000 International
Units of sterile Thrombin topical (Recombinant)

• One vial diluent (containing 20-mL sterile 0.9%
sodium chloride injection, USP)

• Two sterile needle-free transfer devices

• One sterile 20-mL empty syringe for transfer

SPRAY APPLICATOR CONTENTS:

• One spray pump

• One spray bottle

• One syringe spray tip

• One 20-mL syringe

• One 30-mL bowl

• Two blank labels

• Instructions for use

Manufactured for:
Baxter Healthcare Corporation
Deerfield, IL 60015 USA
US License No. 0140
Made in Italy

Baxter Logo
Baxter and Recothrom are registered trademarks
of Baxter International Inc.

20,000 units
NDC: 0338-0330-01

FOR TOPICAL USE ONLY - DO NOT INJECT

RECOTHROM
THROMBIN TOPICAL
(RECOMBINANT)

20,000 units

WITH SPRAY APPLICATOR KIT

Manufactured for:
Baxter Healthcare Corporation
Deerfield, IL 60015 USA
US License No. 0140
Made in Italy

Baxter Logo

07-03-00-1214

FPO

20,000 units
NDC: 0338-0330-01

FOR TOPICAL USE ONLY - DO NOT INJECT

RECOTHROM
THROMBIN TOPICAL
(RECOMBINANT)

20,000 units

WITH SPRAY APPLICATOR KIT

Rx only
Store at 2-25°C (36-77°F).
Do not freeze.
See package insert
Full Prescribing Information.
No components contain latex.
No preservative.

07-03-00-1214

20,000 units
NDC: 0338-0330-01

FOR TOPICAL USE ONLY - DO NOT INJECT

RECOTHROM
THROMBIN TOPICAL
(RECOMBINANT)

20,000 units

WITH SPRAY APPLICATOR KIT

Rx only
Store at 2-25°C (36-77°F).
Do not freeze.
See package insert
Full Prescribing Information.
No components contain latex.
No preservative.

RECOTHROM CONTENTS:
• One single-use vial containing 20,000 International
Units of sterile Thrombin topical (Recombinant)

• One vial diluent (containing 20-mL sterile 0.9%
sodium chloride injection, USP)

• Two sterile needle-free transfer devices

• One sterile 20-mL empty syringe for transfer

SPRAY APPLICATOR CONTENTS:

• One spray pump

• One spray bottle

• One syringe spray tip

• One 20-mL syringe

• One 30-mL bowl

• Two blank labels

• Instructions for use

FPO

FPO

20,000 units
NDC: 0338-0330-01

Baxter Logo

RECOTHROM
THROMBIN TOPICAL
(RECOMBINANT)

20,000 units

WITH SPRAY APPLICATOR KIT

FOR TOPICAL USE ONLY - DO NOT INJECT

Rx only
Store at 2-25°C (36-77°F).
Do not freeze.
See package insert
Full Prescribing Information.
No components contain latex.
No preservative.

RECOTHROM CONTENTS:
• One single-use vial containing 20,000 International
Units of sterile Thrombin topical (Recombinant)

• One vial diluent (containing 20-mL sterile 0.9%
sodium chloride injection, USP)

• Two sterile needle-free transfer devices

• One sterile 20-mL empty syringe for transfer

SPRAY APPLICATOR CONTENTS:

• One spray pump

• One spray bottle

• One syringe spray tip

• One 20-mL syringe

• One 30-mL bowl

• Two blank labels

• Instructions for use